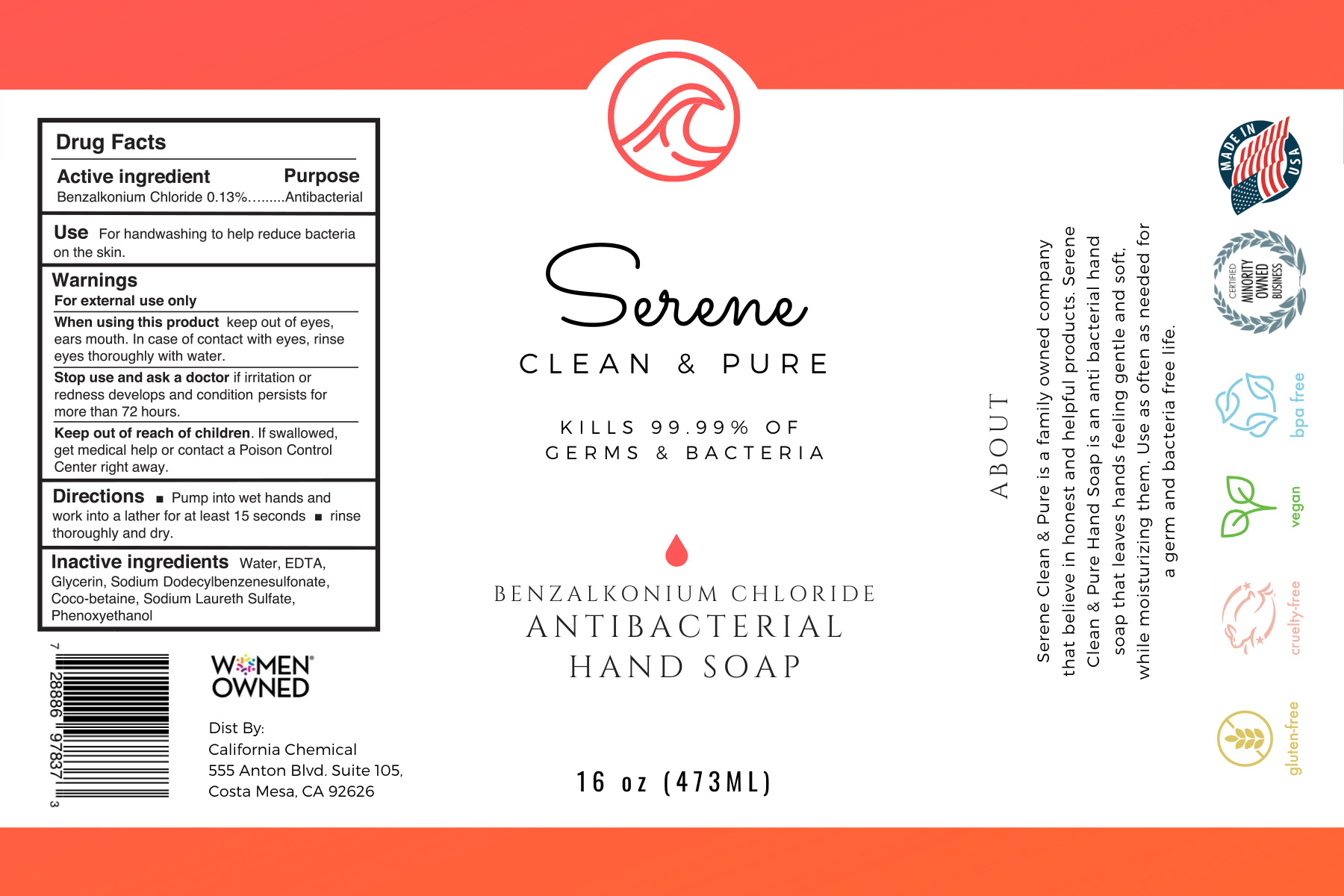 DRUG LABEL: Serene Clean and Pure Antibacterial Hand
NDC: 78643-200 | Form: LIQUID
Manufacturer: Serene Clean & Pure LLC
Category: otc | Type: HUMAN OTC DRUG LABEL
Date: 20200709

ACTIVE INGREDIENTS: BENZALKONIUM CHLORIDE 0.13 g/100 mL
INACTIVE INGREDIENTS: GLYCERIN 1.45 mL/100 mL; WATER; EDETIC ACID; SODIUM LAURETH SULFATE; SODIUM DODECYLBENZENESULFONATE; COCO-BETAINE; PHENOXYETHANOL

Serene Clean & Pure Antibacterial Hand Soap

Active ingredient

Benzalkonium Chloride 0.13%

Purpose

Antibacterial

Use

For handwashing to help reduce bacteria on the skin

Warnings

For external use only.

When using this product

keep out of eyes, ears, and mouth. In case of contact with eyes, rinse eyes thoroughly with water.

Stop use and ask a doctor

if irritation or redness develops and condition persists for more than 72 hours.

Keep out of reach of children.

If swallowed, get medical help or contact a Poison Control Center right away.

Directions

- Pump into wet hands and work into a lather for at least 15 seconds
- Rinse thoroughly and dry

Inactive ingredients

Water, EDTA, Glycerin, Sodium Dodecylbenzenesulfonate, Coco-betaine, Sodium Laureth Sulfate, Phenoxyethanol

Package Label - Principal Display Panel

Serene Clean & Pure

Kills 99.99% of Germs & Bacteria

Benzalkonium Chloride

Antibacterial Hand Soap

16 fl oz

www.serenepure.com

ABOUT

Serene Clean & Pure is a family owned company that believes in honest and helpful products.

Serene Clean & Pure hand soap is an antibacterial hand soap that leaves hands feeling gentle and soft, while moisturizing them. Use as often as needed for a germ and bacteria free life

Distributed by:

Serene Clean & Pure

555 Anton Blvd. Suite 105

Costa Mesa, CA 92626